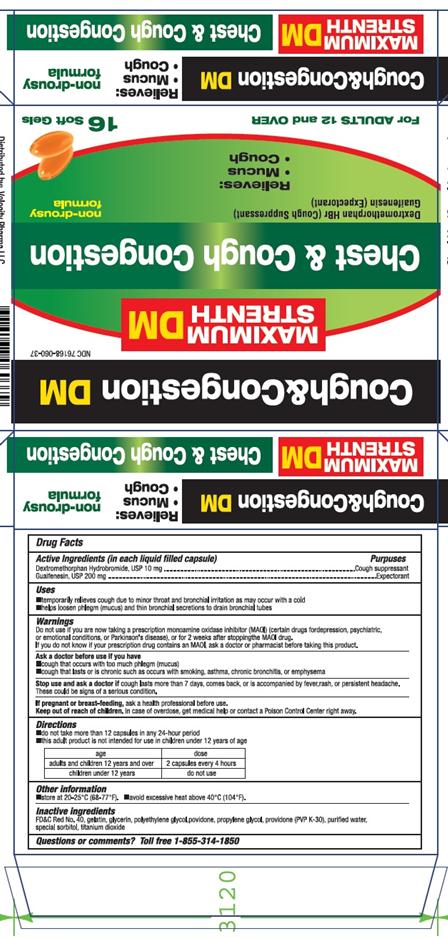 DRUG LABEL: Cough and Congestion DM
NDC: 76168-060 | Form: CAPSULE, LIQUID FILLED
Manufacturer: Velocity Pharma
Category: otc | Type: HUMAN OTC DRUG LABEL
Date: 20160906

ACTIVE INGREDIENTS: DEXTROMETHORPHAN HYDROBROMIDE 10 mg/1 1; GUAIFENESIN 200 mg/1 1
INACTIVE INGREDIENTS: GELATIN; GLYCERIN; POLYETHYLENE GLYCOL 1000; POVIDONE; POVIDONE K30; PROPYLENE GLYCOL; FD&C RED NO. 40; SORBITOL; TITANIUM DIOXIDE

Dextromethorphan HBr (Cough Supressant)

Active Ingredient

(in each liquid filled capsule)

Dextromethorphan Hydrobromide, USP 10mg

Guaifenesin, USP 200mg

Purpose

Cough Suppressant

Expectorant

Uses

- Temporarily relieves cough due minor throat and bronchial irritation as may occur with a cold
- Helps loosen phlegm (mucus) and thin bronchial secretions to drain bronchial tubes

Directions

- Do not take more than 12 capsules in any 24 hour period
- This adult product is not intend for use in children under 12 years of age
  Age | dose
  Adults and children 12 years and over | 2 capsules every 4 hours
  Children under 12 years | Do not use

Warnings

Do not use if you are now taking a prescription monoamine oxidase inhibitor (MAOI) (certain drugs for depression, psychiatric, or emotional conditions or parkinson’s disease) or for 2 weeks after stopping the MAOI drug.

If you do not know if your prescription drug contains an MAOI, ask a doctor or pharmacist before taking this product.

Ask a doctor before use if you have

- cough that occurs with too much phlegm(mucus)
- cough that lasts or is chronic such as occur with smoking, asthma, chronic bronchitis, or emphysema
  Stop use and ask a doctor if cough lasts more than 7 days, comes back, or is accompanied by fever, rash, or persistent headache. This could be signs of a serious condition.
  If pregnant or breast-feeding, ask a health professional before use.

Keep out of reach of children.

In case of overdose, get medical help or contact a Poison Control Center right away.

Other Information

- store at 20-25 °C(68-77 °F)
- avoid excessive heat above 40 °C (104°F)

Inactive Ingredients

FD&C Red No 40, gelatin, glycerin, polyethylene glycol, povidone, propylene glycol, providone (PVP K-30), purified water, special sorbitol, titanium dioxide

Questions or Comments

Toll free 1-855-314-1850

PACKAGE LABEL.PRINCIPAL DISPLAY PANEL

Cough and Congestion DM,

NDC:76168-060-37 16 Softgel Liquid filled